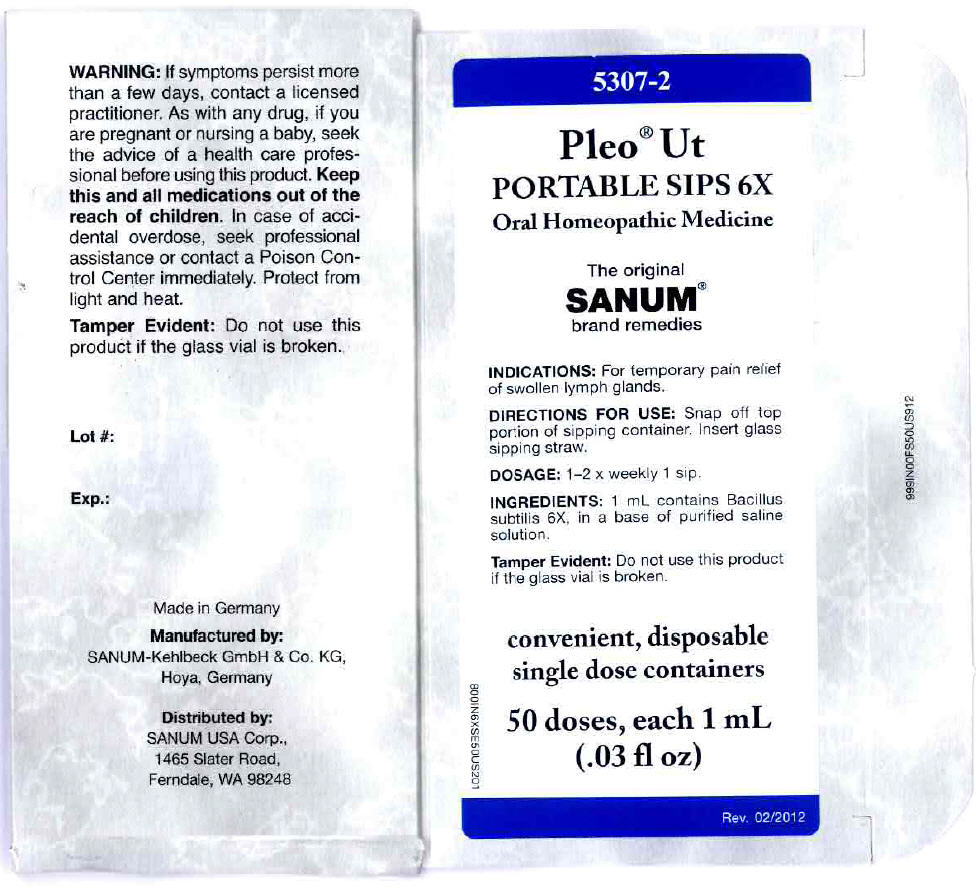 DRUG LABEL: Pleo Ut
NDC: 60681-5307 | Form: LIQUID
Manufacturer: Sanum Kehlbeck GmbH & Co. KG
Category: homeopathic | Type: HUMAN OTC DRUG LABEL
Date: 20130805

ACTIVE INGREDIENTS: bacillus subtilis 6 [hp_X]/1 mL
INACTIVE INGREDIENTS: water; sodium chloride

Pleo® Ut
PORTABLE SIPS 6X

PURPOSE

Oral Homeopathic Medicine

50 doses, each 1 mL
(.03 fl oz)

INDICATIONS

For temporary pain relief of swollen lymph glands.

DIRECTIONS FOR USE

Snap off top portion of sipping container. Insert glass sipping straw.

DOSAGE

1-2 × weekly 1 sip.

INGREDIENTS

INACTIVE INGREDIENT

1 mL contains Bacillus subtilis 6X, in a base of purified saline solution.

WARNING

If symptoms persist more than a few days, contact a licensed practitioner. As with any drug, if you are pregnant or nursing a baby, seek the advice of a health care professional before using this product.

KEEP OUT OF REACH OF CHILDREN

Keep this and all medications out of the reach of children. In case of accidental overdose, seek professional assistance or contact a Poison Control Center immediately.

STORAGE AND HANDLING

Protect from light and heat.

Tamper Evident

Do not use this product if the glass vial is broken or if imprinted security strip on carton is torn.

Made in Germany

Distributed by:
SANUM USA Corp.
1465 Slater Road
Ferndale, WA 98248

Manufactured By:
Sanum-Kehlbeck GmbH & Co. KG

Rev. 10/2002

PRINCIPAL DISPLAY PANEL - 1 mL Vial Carton

5307-2

Pleo® Ut
PORTABLE SIPS 6X

Oral Homeopathic Medicine

The original
SANUM®
brand remedies

INDICATIONS: For temporary pain relief
of swollen lymph glands.

DIRECTIONS FOR USE: Snap off top
portion of sipping container. Insert glass
sipping straw.

DOSAGE: 1–2 x weekly 1 sip.

INGREDIENTS: 1 mL contains Bacillus
subtilis 6X, in a base of purified saline
solution.

Tamper Evident: Do not use this product
if the glass vial is broken.

convenient, disposable
single dose containers

50 doses, each 1 mL
(.03 fl oz)

Rev. 02/2012

800IN6XSE50US201